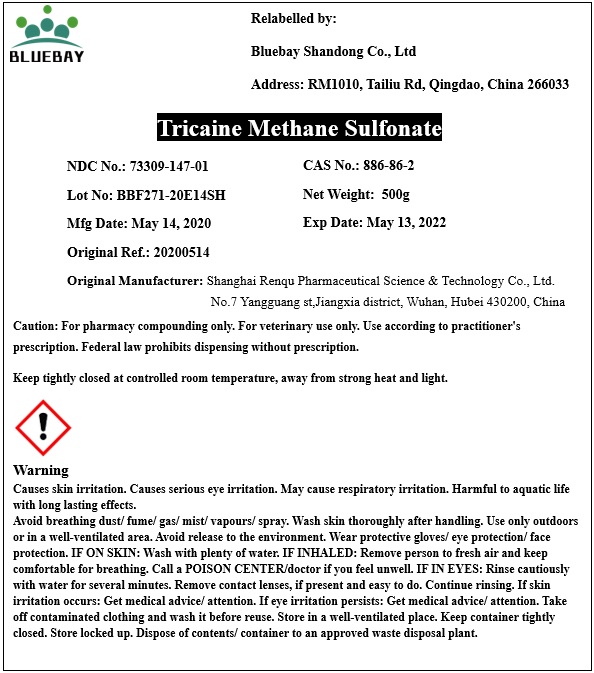 DRUG LABEL: Tricaine Methane Sulfonate
NDC: 73309-147 | Form: POWDER
Manufacturer: BLUEBAY SHANDONG CO.,LTD
Category: other | Type: BULK INGREDIENT
Date: 20200617

ACTIVE INGREDIENTS: TRICAINE 1 g/1 g

Tricaine Methane Sulfonate